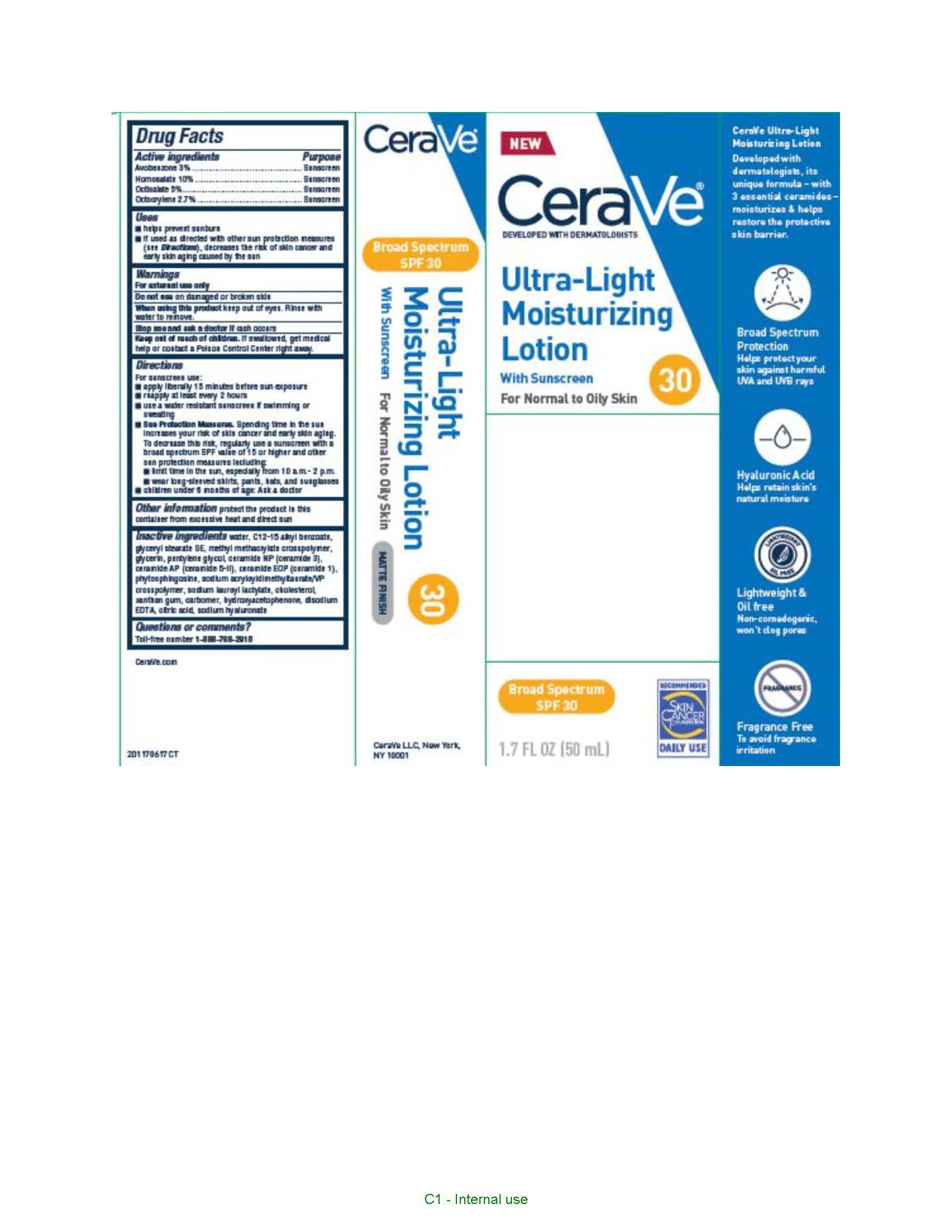 DRUG LABEL: CeraVe Developed with Dermotologists Ultra Light Moisturizing Broad Spectrum SPF 30
NDC: 49967-517 | Form: LOTION
Manufacturer: L'Oreal USA Products Inc
Category: otc | Type: HUMAN OTC DRUG LABEL
Date: 20231231

ACTIVE INGREDIENTS: AVOBENZONE 30 mg/1 mL; HOMOSALATE 100 mg/1 mL; OCTISALATE 50 mg/1 mL; OCTOCRYLENE 27 mg/1 mL
INACTIVE INGREDIENTS: WATER; ALKYL (C12-15) BENZOATE; GLYCERYL STEARATE SE; GLYCERIN; PENTYLENE GLYCOL; CERAMIDE NP; CERAMIDE AP; CERAMIDE 1; PHYTOSPHINGOSINE; SODIUM LAUROYL LACTYLATE; CHOLESTEROL; XANTHAN GUM; CARBOXYPOLYMETHYLENE; HYDROXYACETOPHENONE; EDETATE DISODIUM; CITRIC ACID MONOHYDRATE; HYALURONATE SODIUM

Drug Facts

Active ingredients

Avobenzone 3%

Homosalate 10%

Octisalate 5%

Octocrylene 2.7%

Purpose

Sunscreen

Uses

- helps prevent sunburn
- if used as directed with other sun protection measures (see Directions), decreases the risk of skin cancer and early skin aging caused by the sun

Warnings

For external use only

Do not use

on damaged or broken skin

When using this product

keep out of eyes. Rinse with water to remove.

Stop use and ask a doctor if

rash occurs

Keep out of reach of children.

If swallowed, get medical help or contact a Poison Control Center right away.

Directions

For sunscreen use:

- apply liberally 15 minutes before sun exposure
- reapply at least every 2 hours
- use a water resistant sunscreen if swimming or sweating
- Sun Protection Measures. Spending time in the sun increases your risk of skin cancer and early skin aging. To decrease this risk, regularly use a sunscreen with a broad spectrum SPF value of 15 or higher and other sun protection measures including:
- limit time in the sun, especially from 10 a.m. - 2 p.m.
- wear long-sleeved shirts, pants, hats, and sunglasses
- Children under 6 months of age: Ask a doctor

Other Information

protect the product in this container from excessive hear and direct sun

Inactive ingredient

water, C12-15 alkyl benzoate, glyceryl stearate SE, methyl methacrylate crosspolymer, glycerin, pentylene glycol, ceramide NP (ceramide 3), ceramide AP (ceramide 6-II), ceramide EOP (ceramide 1), phytosphingosine, sodium acryloyldimethyltaurate/VP crosspolymer, sodium lauroyl lactylate, cholesterol, xanthan gum, carbomer, hydroxyacetophenone, disodium EDTA, citric acid, sodium hyaluronate

Questions or comments?

Toll-free number 1-888-768-2915